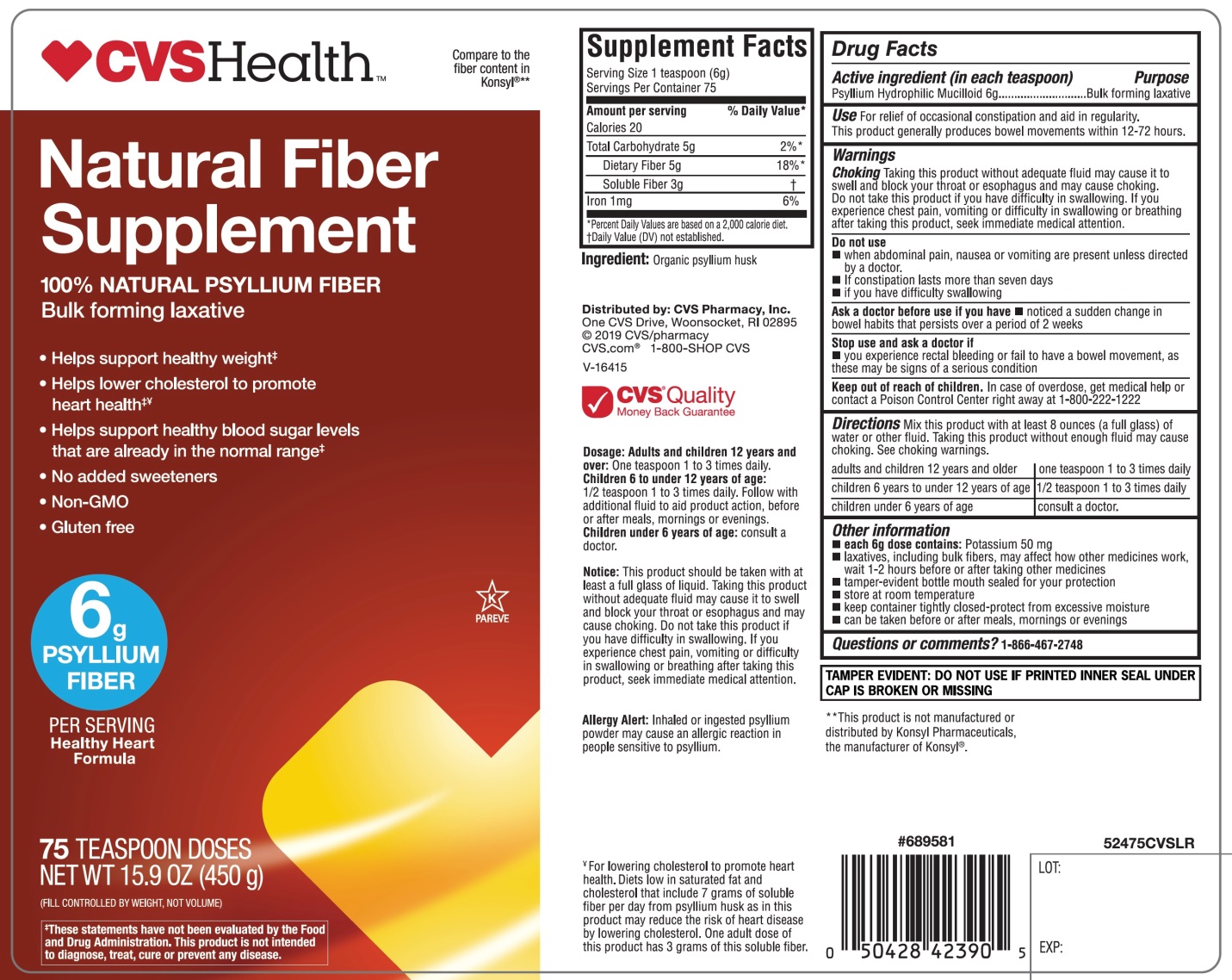 DRUG LABEL: CVS Health
NDC: 69842-524 | Form: POWDER
Manufacturer: CVS Pharmacy,Inc.
Category: otc | Type: HUMAN OTC DRUG LABEL
Date: 20251208

ACTIVE INGREDIENTS: PSYLLIUM HUSK 6 g/6 g
INACTIVE INGREDIENTS: WATER

CVS Health Natural Fiber Supplement 100% Natural Psyllium Fiber Supplement 75 Teaspoon Doses

Active Ingredient (in each dose)

Psyllium Hydrophilic Mucilloid 6 grams

Purpose

Bulk-Forming Laxative

Use

For relief of occasional constipation and to induce regularity. Generally produces bowel movements within 12-72 hours.

Warnings

Allergy alert:As with any natural grain product, inhaled or ingested psyllium powder may cause an allergic reaction in people sensitive to psyllium.

Choking Taking this product without adequate fluid may cause it to swell and block your throat or esophagus and may cause choking. Do not take this product if you have difficulty in swallowing. If you experience chest pain, vomiting or difficulty in swallowing or breathing after taking this product, seek immediate medical attention.

Do not use

- when abdominal pain, nausea or vomiting are present unless directed by a doctor.
- If constipation lasts more than seven days
- If you have difficulty swallowing

Ask a doctor before use if you have

- notices a sudden change in bowel habits that persists over a period of two weeks

Stop use and ask a doctor if

- you experience rectal bleeding or you fail to have a bowel movement as these may be signs of a serious condition.

Keep out of reach of children.

In case of overdose, get medical help or contact a Poison Control Center right away at 1-800-222-1222

Directions

Mix this product (child or adult dose) with at least 8 ounces (a full glass) of water or other fluid. Taking this product without enough fluid may cause choking. See choking warnings.

Adults and children 12 years and older | One teaspoon 1 to 3 times daily
Children 6 years to under 12 years of age | ½ teaspoon 1 to 3 times daily
Childre4n under 6 years of age | Consult a doctor

Other Information

- each 6.0 gram dose contains:Potassium 50 mg
- Laxatives, including bulk fibers, may affect how other medicines work, wait 1-2 hours before or after taking other medicines.
- tamper-evident bottle mouth sealed for your protection
- store at room temperature
- keep container tightly closed-protect from excessive moisture
- can be taken 1 to 3 times daily, before or after meals, mornings or evening

Inactive Ingredients

water

Principal Display Panel

CVS Health™

*Compare to active ingredients in Konsyl Original Formula®

NDC# 69842-524-75

Natural Fiber Supplement

100% Natural Psyllium Fiber

Fiber Supplement

Helps lower cholesterol to promote heart health

Helps Support

- Diabetes management
- Digestive health
- Healthy weight

6g

FIBER

Healthy Heart Formula

75 TEASPOON DOSES

NET WT 450 g (15.9 OZ)

(FILL CONTROLLED BY WEIGHT, NOT VOULUME)

Do not discard powder into any plumbing systems.

†These statement have not been evaluated by the Food and Drug Administration. To diagnose, treat cure or prevent any disease.

*This product is not manufactured or distributed by Konsyl Pharmaceuticals, the manufactured of Konsyl®

CVS®Quality

Money Back Guarantee

Distributed by: CVS Pharmacy, Inc.

One CVS Drive, Woonsocket, RI 02895

© 2019 CVS/pharmacy

CVS.com®1-800-SHOP CVS